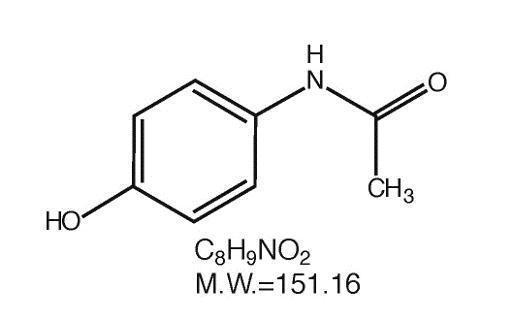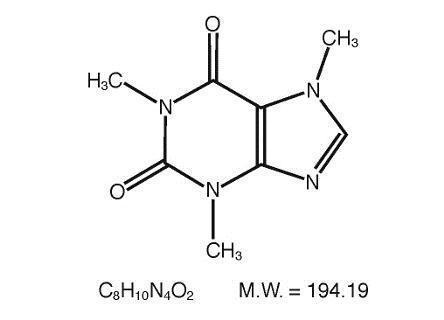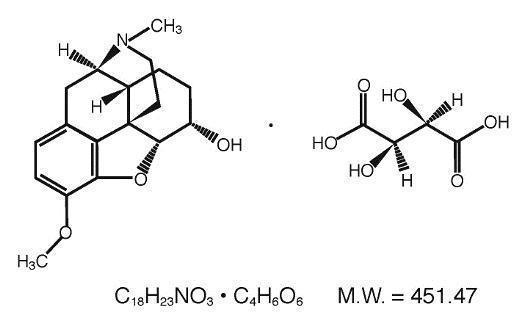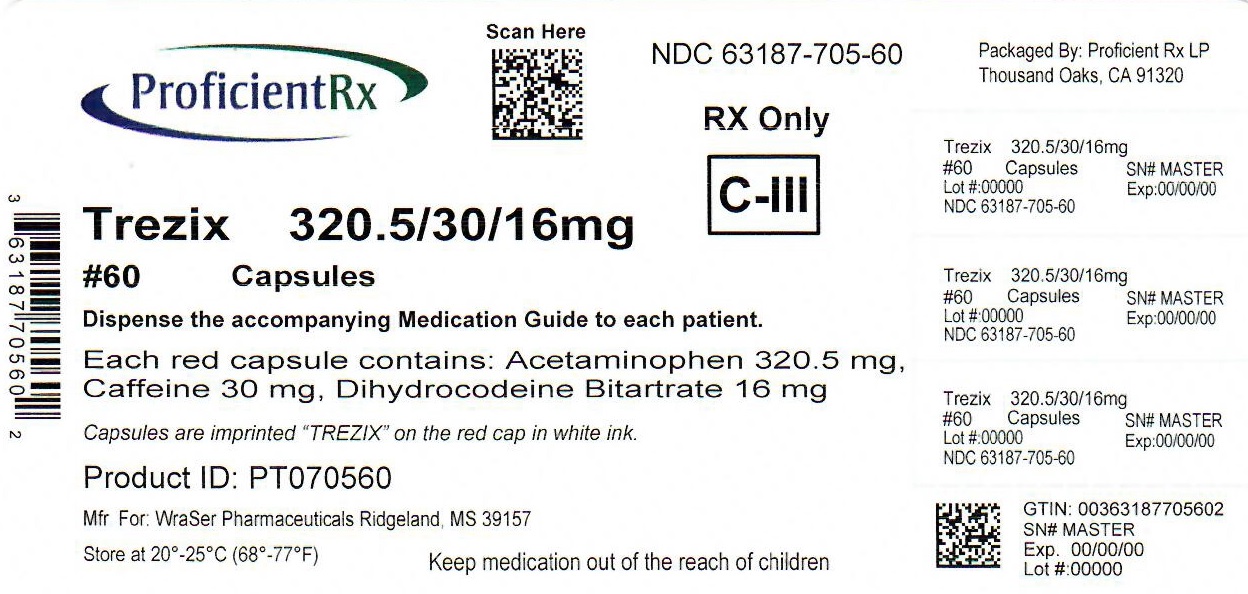 DRUG LABEL: Trezix
NDC: 63187-705 | Form: CAPSULE
Manufacturer: Proficient Rx LP
Category: prescription | Type: HUMAN PRESCRIPTION DRUG LABEL
Date: 20220502
DEA Schedule: CIII

ACTIVE INGREDIENTS: ACETAMINOPHEN 320.5 mg/1 1; CAFFEINE 30 mg/1 1; DIHYDROCODEINE BITARTRATE 16 mg/1 1
INACTIVE INGREDIENTS: CROSPOVIDONE (120 .MU.M); MAGNESIUM STEARATE; CROSPOVIDONE; STARCH, CORN; STEARIC ACID; FD&C RED NO. 40; GELATIN, UNSPECIFIED

TREZIX™ Capsules

Acetaminophen, Caffeine and Dihydrocodeine Bitartrate

320.5 mg / 30 mg / 16 mg
Rx Only CIII

BOXED WARNING

WARNING: Death Related to Ultra-Rapid Metabolism of Codeine to Morphine

Respiratory depression and death have occurred in children who received codeine following tonsillectomy and/or adenoidectomy and had evidence of being ultra-rapid metabolizers of codeine due to a CYP2D6 polymorphism.

Hepatotoxicity
Acetaminophen has been associated with cases of acute liver failure, at times resulting in liver transplant and death. Most of the cases of liver injury are associated with the use of acetaminophen at doses that exceed 4000 milligrams per day, and often involve more than one acetaminophen containing product.

DESCRIPTION:

TREZIX™ capsules are supplied in capsule form for oral administration.
Each red capsule contains:
Acetaminophen...........................................320.5 mg
Caffeine ..........................................................30 mg
Dihydrocodeine bitartrate ...............................16 mg

Acetaminophen (4'-hydroxyacetanilide), a slightly bitter, white, odorless, crystalline powder, is a non-opiate, non-salicylate analgesic and antipyretic. It has the following structural formula:

Caffeine (1,3,7-trimethylxanthine), a bitter, white crystalline powder or white glistening needles, is a central nervous system stimulant. It has the following structural formula:

Dihydrocodeine Bitartrate (4,5 _-epoxy-3-methoxy-17-methylmorphinan-6 _-ol (+)-tartrate), an odorless, fine white powder is an opioid analgesic. It has the following structural formula:
In addition, each capsule contains the following inactive ingredients: crospovidone, magnesium stearate, povidone, pregelatinized starch, stearic acid. The capsule is composed of FD&C Red #40, and gelatin. Imprinting ink is composed of ammonium hydroxide, isopropyl alcohol, n-butyl alcohol, pharmaceutical glaze (modified) in SD-45, propylene glycol, simethicone, and titanium dioxide.

CLINICAL PHARMACOLOGY:

TREZIX™ capsules contain dihydrocodeine which is a semi-synthetic narcotic analgesic related to codeine, with multiple actions qualitatively similar to those of codeine; the most prominent of these involve the central nervous system and organs with smooth muscle components. The principal action of therapeutic value is analgesia.

This combination product also contains acetaminophen, a non-opiate, non-salicylate analgesic and antipyretic. This combination product contains caffeine as an analgesic adjuvant. Caffeine is also a CNS and cardiovascular stimulant.

INDICATIONS AND USAGE:

TREZIX™ (acetaminophen, caffeine, and dihydrocodeine bitartrate) capsulesare indicated for the relief of moderate to moderately severe pain.

CONTRAINDICATIONS:

Dihydrocodeine-containing products are contraindicated for postoperative pain management in children who have undergone tonsillectomy and/or adenoidectomy.

This combination product is contraindicated in patients with hypersensitivity to dihydrocodeine, codeine, acetaminophen, caffeine, or any of the inactive components listed above, or any situation where opioids are contraindicated including significant respiratory depression (in unmonitored settings or in the absence of resuscitative equipment), acute or severe bronchial asthma or hypercapnia, and paralytic ileus.

WARNINGS:

Hepatotoxicity:
Acetaminophen has been associated with cases of acute liver failure, at times resulting in liver transplant and death. Most of the cases of liver injury are associated with the use of acetaminophen at doses that exceed 4000 milligrams per day, and often involve more than one acetaminophen containing product. The excessive intake of acetaminophen may be intentional to cause self-harm or unintentional as patients attempt to obtain more pain relief or unknowingly take other acetaminophen-containing products.
The risk of acute liver failure is higher in individuals with underlying liver disease and in individuals who ingest alcohol while taking acetaminophen.
Instruct patients to look for acetaminophen or APAP on package labels and not to use more than one product that contains acetaminophen. Instruct patients to seek medical attention immediately upon ingestion of more than 4000 milligrams of acetaminophen per day, even if they feel well.

Serious Skin Reactions
Rarely, acetaminophen may cause serious skin reactions such as acute generalized exanthematous pustulosis (AGEP), Stevens-Johnson Syndrome (SJS), and toxic epidermal necrolysis (TEN), which can be fatal. Patients should be informed about the signs of serious skin reactions, and use of the drug should be discontinued at the first appearance of skin rash or any other sign of hypersensitivity.

Death Related to Ultra-Rapid Metabolism of Codeine to Morphine:

Respiratory depression and death have occurred in children who received codeine in the postoperative period following tonsillectomy and/or adenoidectomy and had evidence of being ultra-rapid metabolizers of codeine (i.e., multiple copies of the gene for cytochrome P450 isoenzyme 2D6 or high morphine concentrations). Deaths have also occurred in nursing infants who were exposed to high levels of morphine in breast milk because their mothers were ultra-rapid metabolizers of codeine [see Error! Hyperlink reference not valid.].

Some individuals may be ultra-rapid metabolizers because of a specific CYP2D6 genotype (gene duplications denoted as *1/*1xN or *1/*2xN). The prevalence of this CYP2D6 phenotype varies widely and has been estimated at 0.5 to 1% in Chinese and Japanese, 0.5 to 1% in Hispanics, 1 to 10% in Caucasians, 3% in African Americans, and 16 to 28% in North Africans, Ethiopians, and Arabs. Data are not available for other ethnic groups. These individuals convert dihydrocodeine into its active metabolite, dihydromorphine, more rapidly and completely than other people. This rapid conversion results in higher than expected serum dihydromorphine levels. Even at labeled dosage regimens, individuals who are ultra-rapid metabolizers may have life-threatening or fatal respiratory depression or experience signs of overdose (such as extreme sleepiness, confusion, or shallow breathing) [see Overdosage].

Children with obstructive sleep apnea who are treated with codeine for post-tonsillectomy and/or adenoidectomy pain may be particularly sensitive to the respiratory depressant effects of codeine that has been rapidly metabolized to morphine. Dihydrocodeine-containing products are contraindicated for post-operative pain management in all pediatric patients undergoing tonsillectomy and/or adenoidectomy [see Contraindications].

When prescribing dihydrocodeine-containing products, healthcare providers should choose the lowest effective dose for the shortest period of time and inform patients and caregivers about these risks and the signs of morphine overdose [see Overdosage].

Hypersensitivity/Anaphylaxis:
There have been post-marketing reports of hypersensitivity and anaphylaxis associated with use of acetaminophen. Clinical signs included swelling of the face, mouth, and throat, respiratory distress, urticarial, rash, pruritus, and vomiting. There were infrequent reports of life-threatening anaphylaxis requiring emergency medical attention. Instruct patients to discontinue TREZIX™ immediately and seek medical care if they experience these symptoms. Do not prescribe TREZIX™ for patients with acetaminophen allergy.
Usage in Ambulatory Patients:
Dihydrocodeine may impair the mental and/or physical abilities required for the performance of potentially hazardous tasks such as driving a car or operating machinery.
Respiratory Depression:
Respiratory depression is the most dangerous acute reaction produced by opioid agonist preparations, although it is rarely severe with usual doses. Opioids decrease the respiratory rate, tidal volume, minute ventilation, and sensitivity to carbon dioxide. Respiratory depression occurs most frequently in elderly or debilitated patients, usually after large initial doses in nontolerant patients, or when opioids are given in conjunction with other agents that depress respiration. This combination product should be used with caution in patients with significant chronic obstructive pulmonary disease or cor pulmonale and in patients with a substantially decreased respiratory reserve, hypoxia hypercapnia, or respiratory depression. In such patients, alternative non-opioid analgesics should be considered, and opioids should be administered only under careful medical supervision at the lowest effective dose.
Head Injury:
This combination product should be used cautiously in the presence of head injury or increased intracranial pressure. The effects of opioids on pupillary response and consciousness may obscure neurologic signs of increases in intracranial pressure in patients with head injuries. The respiratory depressant effects including carbon dioxide retention and secondary elevation of cerebrospinal fluid pressure may be markedly exaggerated in the presence of head injury, intracranial lesions, or other causes of increased intracranial pressures.
Hypotensive Effect:
Dihydrocodeine, like all opioid analgesics, may cause hypotension in patients whose ability to maintain blood pressure has been compromised by a depleted blood volume or who receive concurrent therapy with drugs such as phenothiazines or other agents which compromise vasomotor tone. Acetaminophen, caffeine and dihydrocodeine bitartrate capsules may produce orthostatic hypotension in ambulatory patients. This combination product should be administered with caution to patients in circulatory shock, since vasodilation produced by the drug may further reduce cardiac output and blood pressure.
Drug Dependence:
Dihydrocodeine can produce drug dependence of the codeine type and has the potential of being abused (See DRUG ABUSE AND DEPENDENCE).

PRECAUTIONS:

General:

Selection of patients for treatment with TREZIX™ (acetaminophen, caffeine, and dihydrocodeine bitartrate) capsules should be governed by the same principles that apply to the use of similar opioid/non-opioid fixed combination analgesics. As with any such opioid analgesic, the dosing regimen should be adjusted for each patient (See DOSAGE AND ADMINISTRATION). This combination product should be used with caution in elderly or debilitated patients or those with any of the following conditions: acute alcoholism; adrenocortical insufficiency (e.g., Addison's disease); asthma; central nervous system depression or coma; chronic obstructive pulmonary disease; decreased respiratory reserve (including emphysema, severe obesity, cor pulmonale, or kyphoscoliosis); delirium tremens; head injury; hypotension; increased intracranial pressure; myxedema or hypothyroidism; prostatic hypertrophy or urethral stricture; and toxic psychosis. The benefits and risks of using opioids in patients taking monoamine oxidase inhibitors and in those with a history of drug abuse should be carefully considered. The administration of an analgesic containing an opioid may obscure the diagnosis or clinical course in patients with acute abdominal conditions. This combination product may aggravate convulsions in patients with convulsive disorders and, like all opioids, may induce or aggravate seizures in some clinical settings.

Acetaminophen is relatively non-toxic at therapeutic doses, but should be used with caution in patients with severe renal or hepatic disease. Care should be observed when using large doses of acetaminophen in malnourished patients or those with a history of chronic alcohol abuse because they may be more susceptible to hepatic damage similar to that observed with toxic overdosage. Caffeine in high doses may produce central nervous system and cardiovascular stimulation and gastrointestinal irritation.

Drug Interactions:

Dihydrocodeine with Other Central Nervous System Depressants:
Patients receiving other opioid analgesics, sedatives or hypnotics, muscle relaxants, general anesthetics, centrally acting anti-emetics, phenothiazines or other tranquilizers, or alcohol concomitantly with this combination product may exhibit additive depressant effects on the central nervous system. When such combined therapy is contemplated, the dose of one or both agents should be reduced.
Dihydrocodeine with Monoamine Oxidase Inhibitors:
Dihydrocodeine, like all opioid analgesics, interacts with monoamine oxidase inhibitors causing central nervous system excitation and hypertension.
Dihydrocodeine with Mixed Agonist/Antagonist Opioid Analgesics:
Agonist/antagonist analgesics (i.e., pentazocine, nalbuphine, butorphanol and buprenorphine) may reduce the analgesic effect of this combination product.
Acetaminophen Drug Interactions:
Chronic and excessive consumption of alcohol may increase the hepatotoxic risk of acetaminophen. The potential for hepatotoxicity with acetaminophen also may be increased in patients receiving anticonvulsants that induce hepatic microsomal enzymes (including phenytoin, barbiturates, and carbamazepine) or isoniazide. Chronic ingestion of large doses of acetaminophen may slightly potentiate the effects of warfarin-
and indandione- derivative anticoagulants. Severe hypothermia is possible in patients receiving acetaminophen concomitantly with phenothiazines.
Caffeine Drug Interactions:
Caffeine may enhance the cardiac inotropic effects of beta-adrenergic stimulating agents. Co-administration of caffeine and disulfiram may lead to a substantial decrease in caffeine clearance. Caffeine may increase the metabolism of other drugs such as phenobarbital and aspirin. Caffeine accumulation may occur when products or foods containing caffeine are consumed concomitantly with quinolones such as ciprofloxacin.

Information for Patients

Patients receiving TREZIX™ (acetaminophen, caffeine, and dihydrocodeine bitartrate) capsules should be given the following information:

1. Do not take TREZIX™ if you are allergic to any of its ingredients.
2. If you develop signs of allergy such as a rash or difficulty breathing stop taking TREZIX™ and contact your healthcare provider immediately.
3. Do not take more than 4000 milligrams of acetaminophen per day. Call your doctor if you took more than the recommended dose.
4. Patients should be advised that TREZIX™ capsules may impair the mental or physical abilities required for the performance of potentially hazardous tasks such as driving a car or operating machinery.
5. Patients should be advised to report adverse experiences occurring during therapy.
6. Patients should be advised not to adjust the dose of TREZIX™ capsules without consulting the prescribing professional.
7. Patients should not combine TREZIX™ capsules with alcohol or other central nervous system depressants (sleep aids, tranquilizers) except by the orders of the prescribing physician, because additive effects may occur.
8. Women of childbearing potential who become, or are planning to become, pregnant should be advised to consult their physician regarding the effects of analgesics and other drug use during pregnancy on themselves and their unborn child.
9. Patients should be advised that TREZIX™ capsules are a potential drug of abuse. They should protect it from theft, and it should never be given to anyone other than the individual for whom it was prescribed.

Advise patients that some people have a genetic variation that results in dihydrocodeine changing into dihydromorphine more rapidly and completely than other people. Most people are unaware of whether they are an ultra-rapid dihydrocodeine metabolizer or not. These higher-than-normal levels of dihydromorphine in the blood may lead to life-threatening or fatal respiratory depression or signs of overdose such as extreme sleepiness, confusion, or shallow breathing. Children with this genetic variation who were prescribed codeine after tonsillectomy and/or adenoidectomy for obstructive sleep apnea may be at greatest risk based on reports of several deaths in this population due to respiratory depression. Dihydrocodeine-containing products are contraindicated in all children who undergo tonsillectomy and/or adenoidectomy. Advise caregivers of children receiving dihydrocodeine-containing products for other reasons to monitor for signs of
respiratory depression.

Advise patients that nursing mothers taking dihydrocodeine can also have higher dihydromorphine levels in their breast milk if they are ultra-rapid metabolizers. These higher levels of dihydromorphine in breast milk may lead to life-threatening or fatal side effects in nursing babies. Advise nursing mothers to watch for signs of dihydromorphine toxicity in their infants including increased sleepiness (more than usual), difficulty breastfeeding, breathing difficulties, or limpness. Instruct nursing mothers to talk to the baby’s doctor immediately if they notice these signs and, if they cannot reach the doctor right away, to take the baby to an emergency room or call 911 (or local emergency services).

Pregnancy:

Teratogenic Effects – Pregnancy Category C. Animal reproduction studies have not been conducted with TREZIX™ (acetaminophen, caffeine, and dihydrocodeine bitartrate) capsules. It is also not known whether this combination product can cause fetal harm when administered to pregnant women or can affect reproduction capacity in males and females. This combination product should be given to pregnant women only if clearly needed, especially during the first trimester.

Labor and Delivery:

TREZIX™ (acetaminophen, caffeine, and dihydrocodeine bitartrate) capsules are not recommended for use by women during and immediately before labor and delivery because oral opioids may cause respiratory depression in the newborn.

Nursing Mothers:

Dihydrocodeine bitartrate is secreted into human milk. In women with normal dihydrocodeine metabolism (normal CYP2D6 activity), the amount of dihydrocodeine secreted into human milk is low and dose-dependent. However, some women are ultra-rapid metabolizers of dihydrocodeine. These women achieve higher-than-expected serum levels of dihydrocodeine’s active metabolite, dihydromorphine, leading to higher-than-expected levels of dihydromorphine in breast milk and potentially dangerously high serum dihydromorphine levels in their breastfed infants. Therefore, maternal use of dihydrocodeine can potentially lead to serious adverse reactions, including death, in nursing infants.

The risk of infant exposure to dihydrocodeine and morphine through breast milk should be weighed against the benefits of breastfeeding for both the mother and baby. Caution should be exercised when dihydrocodeine is administered to a nursing woman. If a dihydrocodeine containing product is selected, the lowest dose should be prescribed for the shortest period of time to achieve the desired clinical effect. Mothers using dihydrocodeine should be informed about when to seek immediate medical care and how to identify the signs and symptoms of neonatal toxicity, such as drowsiness or sedation, difficulty breastfeeding, breathing difficulties, and decreased tone, in their baby. Nursing mothers who are ultra-rapid metabolizers may also experience overdose symptoms such as extreme sleepiness, confusion or shallow breathing. Prescribers should closely monitor mother-infant pairs and notify treating pediatricians about the use of dihydrocodeine-containing products during breastfeeding (See Warnings).

Acetaminophen and caffeine are also excreted in breast milk in small amounts. Because of the potential for serious adverse reactions in nursing infants from this combination product, a decision should be made whether to discontinue nursing or to discontinue the drug, taking into account the importance of the drug to the mother.

Pediatric Use:

Safety and effectiveness of TREZIX™ (acetaminophen, caffeine, and dihydrocodeine bitartrate) capsules in pediatric patients have not been established.

Respiratory depression and death have occurred in children with obstructive sleep apnea who received codeine in the post-operative period following tonsillectomy and/or adenoidectomy and had evidence of being ultra-rapid metabolizers of codeine (i.e., multiple copies of the gene for cytochrome P450 isoenzyme CYP2D6 or high morphine concentrations). These children may be particularly sensitive to the respiratory depressant effects of codeine that has been rapidly metabolized to morphine.

Dihydrocodeine-containing products are contraindicated for post-operative pain management in all pediatric patients undergoing tonsillectomy and/or adenoidectomy [see CONTRAINDICATIONS].

Geriatric Use:

TREZIX™ (acetaminophen, caffeine, and dihydrocodeine bitartrate) capsules should be given with caution to the elderly.

Hepatic Impairment:

TREZIX™ (acetaminophen, caffeine, and dihydrocodeine bitartrate) capsules should be given with caution to patients with hepatic insufficiency. Since dihydrocodeine is metabolized by the liver and since acetaminophen potentially causes hepatotoxicity, the effects of this combination product should be monitored closely in such patients.

Renal Impairment:

TREZIX™ (acetaminophen, caffeine, and dihydrocodeine bitartrate) capsules should be used with caution and at reduced dosage in the presence of impaired renal function.

Pancreatic/Biliary Tract Disease:

Opioids may cause spasms of the sphincter of Oddi and should be used with caution in patients with biliary tract disease including pancreatitis.

ADVERSE REACTIONS:

Dihydrocodeine:
The most frequently observed adverse reactions include light-headedness, dizziness, drowsiness, headache, fatigue, sedation, sweating, nausea, vomiting, constipation, pruritus, and skin reactions. With the exception of constipation, tolerance develops to most of these effects. Other reactions that have been observed with dihydrocodeine or other opioids include respiratory depression, orthostatic hypotension, cough suppression, confusion, diarrhea, miosis, abdominal pain, dry mouth, indigestion, anorexia, spasm of biliary tract, and urinary retention. Physical and psychological dependence are possibilities. Hypersensitivity reactions (including anaphylactoid reactions), hallucinations, vivid dreams, granulomatous interstitial nephritis, severe narcosis and acute renal failure have been reported rarely during dihydrocodeine administration.
Acetaminophen:
Acetaminophen in therapeutic doses rarely causes adverse reactions. The most serious adverse reaction is hepatoxicity from overdosage (see OVERDOSAGE). Thrombocytopenia, leukopenia, pancytopenia, neutropenia, thrombocytopenic purpura, and agranulocytosis have been reported in patients receiving acetaminophen or p-aminophenol derivatives. Hypersensitivity reactions including urticarial or erythematous skin reactions, laryngeal edema, angioedema, or anaphylactoid reactions are rare.
Caffeine:
Adverse reactions associated with caffeine use include anxiety, anxiety neurosis, excitement, headaches, insomnia, irritability, lightheadedness, restlessness, tenseness, tremor, extrasystoles, palpitations, tachycardia, diarrhea, nausea, stomach pain, vomiting, diuresis, urticaria, scintillating scotoma, and tinnitus.

DRUG ABUSE AND DEPENDENCE:

This combination product is subject to the provisions of the Controlled Substance Act and has been placed in Schedule III.

Dihydrocodeine can produce drug dependence of the codeine type and therefore has the potential of being abused. Like other opioid analgesics, dihydrocodeine may produce subjected effects other than analgesia (e.g., euphoria, relaxation), which may contribute to abuse by some patients. Psychological dependence, physical dependence, and tolerance may develop upon repeated administration of dihydrocodeine, and it should be prescribed and administered with the same degree of caution appropriate to the use of other oral opioid analgesic medications. Symptoms of dihydrocodeine withdrawal consist of irritability, restlessness, insomnia, diaphoresis, anxiety and palpitations. Prolonged, high intake of caffeine may produce tolerance and habituation. Physical signs of withdrawal, such as headaches, irritation, nervousness, anxiety, and dizziness may occur upon abrupt discontinuation.

OVERDOSAGE:

Following an acute overdosage with TREZIX™ (acetaminophen, caffeine, and dihydrocodeine bitartrate) capsules, toxicity may result from the dihydrocodeine or the acetaminophen. Toxicity due to the caffeine component is less likely, due to the relatively small amounts in this formulation. An overdose is a potentially lethal polydrug overdose situation, and consultation with a regional Poison Control Center is recommended. A listing of the poison control centers can be found in standard references such as the Physician's Desk Reference®.
Signs and Symptoms: Toxicity from dihydrocodeine poisoning include the opioid triad of: pinpoint pupils, respiratory depression, and loss of consciousness. Convulsions, cardiovascular collapse, and death may occur. A single case of acute rhabdomyolysis associated with an overdose of dihydrocodeine has been reported. In acetaminophen overdosage: dose-dependent potentially fatal hepatic necrosis is the most serious adverse effect. Renal tubular necrosis, hypoglycemic coma, and coagulation defects may also occur. Early symptoms following a potentially hepatotoxic overdose may include: nausea, vomiting, diaphoresis, and general malaise. Clinical and laboratory evidence of hepatic toxicity may not be apparent until 48 to 72 hours post ingestion. Acute caffeine poisoning may cause insomnia, restlessness, tremor, delirium, tachycardia, and extrasystoles.
Because overdose information on this combination product is limited, it is unclear which of the signs and symptoms of toxicity would manifest in any particular overdose situation.
Treatment
A single or multiple drug overdose with TREZIX™ (acetaminophen, caffeine, and dihydrocodeine bitartrate) capsules is a potentially lethal polydrug overdose, and consultation with a regional Poison Control Center is recommended. Immediate treatment includes support of cardiorespiratory function and measures to reduce drug absorption. Oxygen, intravenous fluids, and vasopressors, and other supportive measures should be employed as indicated. Assisted or controlled ventilation should also be considered. For respiratory depression due to overdosage or unusual sensitivity to dihydrocodeine, parenteral naloxone is a specific and effective antagonist. Gastric decontamination with activated charcoal should be administered just prior to N-acetylcysteine (NAC) to decrease systemic absorption if acetaminophen ingestion is known or suspected to have occurred within a few hours of presentation. Serum acetaminophen levels should be obtained immediately if the patient presents 4 hours or more after ingestion to assess potential risk of hepatotoxicity; acetaminophen levels drawn less than 4 hours post-ingestion may be misleading. To obtain the best possible outcome, NAC should be administered as soon as possible where impending or evolving liver injury is suspected. Intravenous NAC may be administered when circumstances preclude oral administration.
Vigorous supportive therapy is required in severe intoxication. Procedures to limit the continuing absorption of the drug must be readily performed since the hepatic injury is dose dependent and occurs early in the course of intoxication.

DOSAGE AND ADMINISTRATION:

The usual adult dosage is two (2) TREZIX™ (acetaminophen, caffeine, and dihydrocodeine bitartrate) capsules orally every four (4) hours, as needed. Dosage should be adjusted according to the severity of the pain and the response of the patient. No more than two (2) capsules should be taken in a 4-hour period. No more than five (5) doses, or ten (10) capsules should be taken in a 24-hour period.

HOW SUPPLIED:

TREZIX™ capsules, containing acetaminophen 320.5 mg, caffeine 30 mg and dihydrocodeine bitartrate 16 mg, are supplied in bottles of 30(NDC #63187-705-30), 60(NDC #63187-705-60), 90(NDC #63187-705-90), 100 (NDC #63187-705-00) and 120 capsules (NDC #63187-705-72)

Capsules are imprinted “TREZIX” on the red cap in white ink.

Store at 20°C to 25°C (68°F to 77°F). [see USP Controlled Room Temperature].

Dispense in a tight, light-resistant container with a child-resistant closure. Protect from moisture.

Rx Only

Manufactured for:
WraSer Pharmaceuticals LLC
Ridgeland, MS 39157

Repackaged by:
Proficient Rx LP
Thousand Oaks, CA 91320

13001 Rev. May 2014

Physician’s Desk Reference® is the registered trademark of Thomson Healthcare, Inc.

Trezix 100 Count Bottle

NDC 63187-705-60

TREZIXTM CIII

(acetaminophen, caffeine and dihydrocodeine bitartrate capsules 320.5mg/30mg/16mg)

Rx ONLY

60 CAPSULES

DESCRIPTION:
Each red capsule contains:
Acetaminophen .................................. 320.5 mg
Caffeine ................................................... 30 mg
Dihydrocodeine Bitartrate ....................... 16 mg

USUAL DOSAGE: See package insert for full prescribing information.

WARNING: Keep this and all medications out of the reach of children.

PHARMACIST: Dispense in a tight, light-resistant container with a child-resistant closure. Store at 20° to 25°C (68° to 77°F) [see USP Controlled Room Temperature]. Protect from moisture.

Manufactured for:
WraSer Pharmaceuticals
Ridgeland, MS 39157
www.wraser.com

Repackaged by:
Proficient Rx LP
Thousand Oaks, CA 91320

13001 Rev. 5/14

WraSer PHARMACEUTICALS